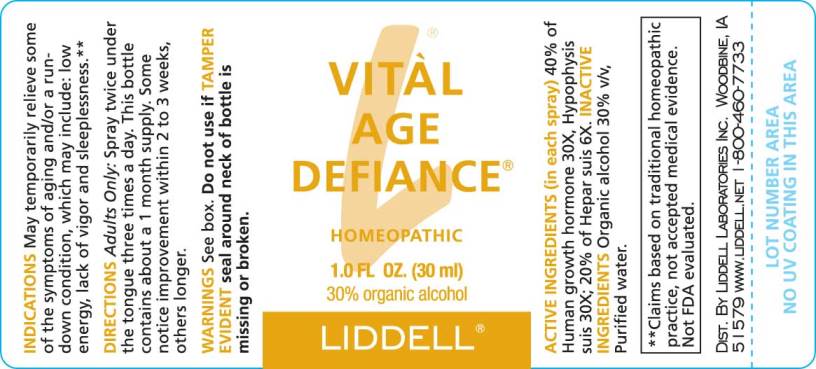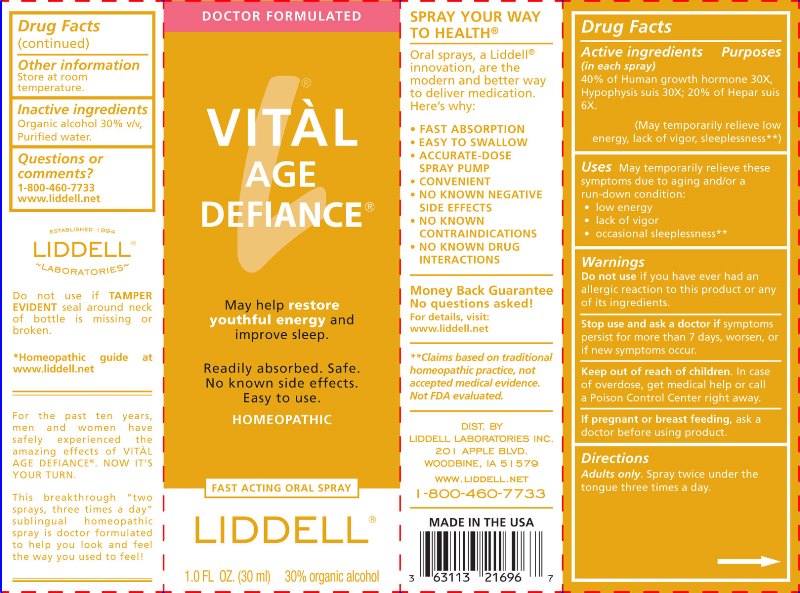 DRUG LABEL: Vital Age Defiance
NDC: 50845-0199 | Form: SPRAY
Manufacturer: Liddell Laboratories, Inc.
Category: homeopathic | Type: HUMAN OTC DRUG LABEL
Date: 20240701

ACTIVE INGREDIENTS: SOMATROPIN 30 [hp_X]/1 mL; SUS SCROFA PITUITARY GLAND 30 [hp_X]/1 mL; PORK LIVER 6 [hp_X]/1 mL
INACTIVE INGREDIENTS: WATER; ALCOHOL

DRUG FACTS:

ACTIVE INGREDIENTS:

(in each spray) 40% of Human growth hormone 30X (2 Parts), Hypophysis suis 30X (2 Parts); 20% of Hepar suis 6X (1 Part).

USES:

May temporarily relieve these symptoms due to aging and/or a run-down condition:

- low energy
- lack of vigor
- occasional sleeplessness.**

**Claims based on traditional homeopathic practice, not accepted medical evidence. Not FDA evaluated.

WARNINGS:

Do not use if you have ever had an allergic reaction to this product or any of its ingredients.

Stop use and ask a doctor if symptoms persist for more than 7 days, worsen, or if new symptoms occur.

Keep out of reach of children. In case of overdose, get medical help or call a Poison Control Center right away.

If pregnant or breast feeding, ask a doctor before use.

Other information: Store at room temperature.

Keep out of reach of children. In case of overdose, get medical help or call a Poison Control Center right away.

DIRECTIONS:

Adults only: Spray twice under the tongue three times a day.

INDICATIONS:

May temporarily relieve these symptoms due to aging and/or a run-down condition:

low energy
lack of vigor
occasional sleeplessness.**

**Claims based on traditional homeopathic practice, not accepted medical evidence. Not FDA evaluated.

INACTIVE INGREDIENTS:

Organic alcohol 30% v/v, Purified water

QUESTIONS:

DIST. BY

LIDDELL LABORATORIES, INC.

201 APPLE BLVD.

WOODBINE, IA 51579

WWW.LIDDELL.NET

1-800-460-7733

PACKAGE LABEL DISPLAY:

DOCTOR FORMULATED

VITAL
AGE
DEFIANCE

May help restore youthful energy and improve sleep.

Readily absorbed. Safe. No known side effects. Easy to use.

HOMEOPATHIC

FAST ACTING ORAL SPRAY

LIDDELL
1.0 FL. OZ (30 ml)